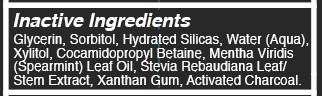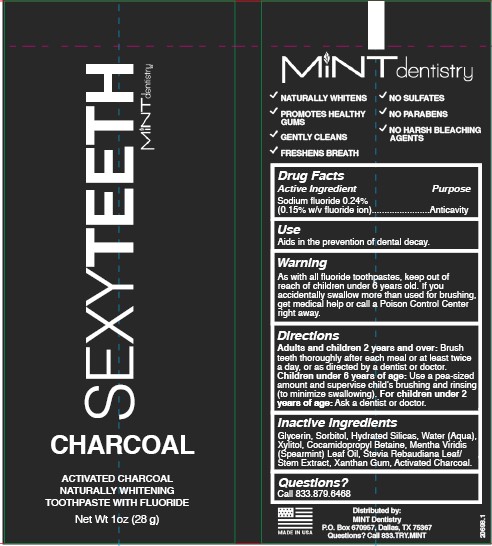 DRUG LABEL: Mint Dentistry
NDC: 73333-115 | Form: PASTE
Manufacturer: Nutrix International, LLC.
Category: otc | Type: HUMAN OTC DRUG LABEL
Date: 20220510

ACTIVE INGREDIENTS: SODIUM FLUORIDE 0.2938 g/113 g
INACTIVE INGREDIENTS: STEVIA REBAUDIUNA LEAF 0.3955 g/113 g; SILICON DIOXIDE 23.73 g/113 g; GLYCERIN 31.753 g/113 g; WATER 16.3285 g/113 g; COCAMIDOPROPYL BETAINE 1.8532 g/113 g; ACTIVATED CHARCOAL 0.565 g/113 g; XYLITOL 11.3 g/113 g; XANTHAN GUM 0.452 g/113 g; SPEARMINT OIL 1.469 g/113 g; SORBITOL 24.86 g/113 g

Mint Dentistry - Charcoal Sexy teeth

ACTIVE INGREDIENT

Sodium fluoride 0.24%

(0.15%w/v fluoride ion)

PURPOSE

Anticavity

INDICATIONS AND USAGE

Aids in the prevention of dental decay.

WARNING

As with all fluoride toothpaste, keep out of reach of children under 6 years old. If you accidentally swallow more than used for brushing, get medical help or call a Poison Control Center right away.

KEEP OUT OF REACH SECTION

Keep out of reach of children under 6 years of age.

DIRECTIONS

Adults and children 2 years and over: Brush teeth thoroughly after each meal or at least twice a day, or as directed by a dentist or doctor.
Children under 6 years of age: Use a pea-sized amount and supervise child's brushing and rinsing (to minimize swallowing). For children under 2 years of age: Ask a dentist or doctor.

INACTIVE INGREDIENTS

Glycerin, Sorbitol, Hydrated Silicas, Water (Aqua), Xylitol, Cocamidopropyl Betaine, Mentha Viridis (Spearmint) Leaf Oil, Stevia Rebaudiana Leaf /Steam Extract, Xanthan Gum, Activated Charcoal.

QUESTIONS?

Call 833.879.6468

Dosage and Administration

Use a pea-sized amount via oral